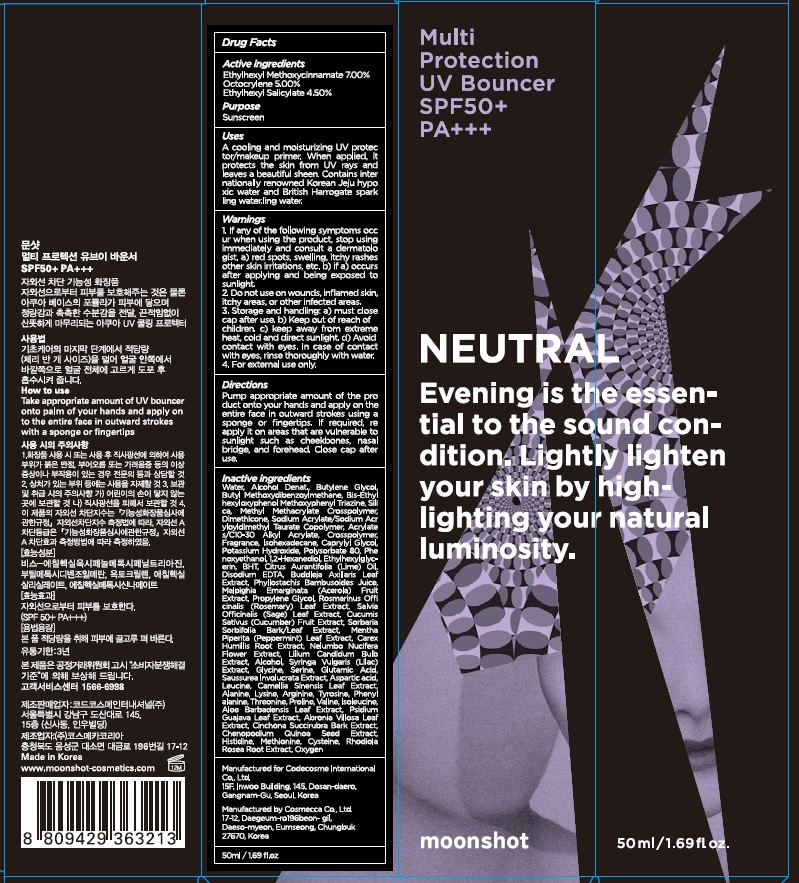 DRUG LABEL: Multi Protection UV Bouncer
NDC: 71786-010 | Form: CREAM
Manufacturer: Codecosme International Co., Ltd.
Category: otc | Type: HUMAN OTC DRUG LABEL
Date: 20171018

ACTIVE INGREDIENTS: Octinoxate 3.5 g/50 mL; Octocrylene 2.5 g/50 mL; Octisalate 2.25 g/50 mL
INACTIVE INGREDIENTS: Water; Butylene Glycol

ACTIVE INGREDIENT

Active ingredients: Ethylhexyl Methoxycinnamate 7.00%, Octocrylene 5.00%, Ethylhexyl Salicylate 4.50%

INACTIVE INGREDIENT

Inactive ingredients: Water, Alcohol Denat., Butylene Glycol, Butyl Methoxydibenzoylmethane, Bis-Ethylhexyloxyphenol Methoxyphenyl Triazine, Silica, Methyl Methacrylate Crosspolymer, Dimethicone, Sodium Acrylate/Sodium Acryloyldimethyl Taurate Copolymer, Acrylates/C10-30 Alkyl Acrylate, Crosspolymer, Fragrance, Isohexadecane, Caprylyl Glycol, Potassium Hydroxide, Polysorbate 80, Phenoxyethanol, 1,2-Hexanediol, Ethylhexylglycerin, BHT, Citrus Aurantifolia (Lime) Oil, Disodium EDTA, Buddleja Axillaris Leaf Extract, Phyllostachis Bambusoides Juice, Malpighia Emarginata (Acerola) Fruit Extract, Propylene Glycol, Rosmarinus Officinalis (Rosemary) Leaf Extract, Salvia Officinalis (Sage) Leaf Extract, Cucumis Sativus (Cucumber) Fruit Extract, Sorbaria Sorbifolia Bark/Leaf Extract, Mentha Piperita (Peppermint) Leaf Extract, Carex Humillis Root Extract, Nelumbo Nucifera Flower Extract, Lilium Candidum Bulb Extract, Alcohol, Syringa Vulgaris (Lilac) Extract, Glycine, Serine, Glutamic Acid, Saussurea Involucrata Extract, Aspartic acid, Leucine, Camellia Sinensis Leaf Extract, Alanine, Lysine, Arginine, Tyrosine, Phenylalanine, Threonine, Proline, Valine, Isoleucine, Aloe Barbadensis Leaf Extract, Psidium Guajava Leaf Extract, Abronia Villosa Leaf Extract, Cinchona Succirubra Bark Extract, Chenopodium Quinoa Seed Extract, Histidine, Methionine, Cysteine, Rhodiola Rosea Root Extract, Oxygen

PURPOSE

Purpose: Sunscreen

WARNINGS

Warnings: 1. If any of the following symptoms occur when using the product, stop using immediately and consult a dermatologist. a) red spots, swelling, itchy rashes other skin irritations, etc. b) if a) occurs after applying and being exposed to sunlight. 2. Do not use on wounds, inflamed skin, itchy areas, or other infected areas. 3. Storage and handling: a) must close cap after use. b) Keep out of reach of children. c) keep away from extreme heat, cold and direct sunlight. d) Avoid contact with eyes. In case of contact with eyes, rinse thoroughly with water. 4. For external use only.

DESCRIPTION

Uses: A cooling and moisturizing UV protector/makeup primer. When applied, it protects the skin from UV rays and leaves a beautiful sheen. Contains internationally renowned Korean Jeju hypoxic water and British Harrogate sparkling water.

Directions: Pump appropriate amount of the product onto your hands and apply on the entire face in outward strokes using a sponge or fingertips. If required, reapply it on areas that are vulnerable to sunlight such as cheekbones, nasal bridge, and forehead. Close cap after use.